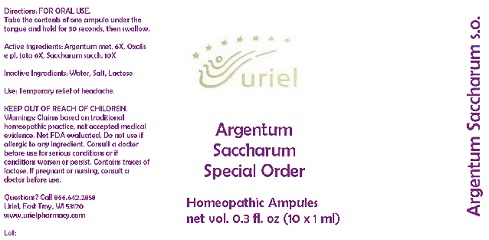 DRUG LABEL: Argentum Saccharum Special Order
NDC: 48951-1329 | Form: LIQUID
Manufacturer: Uriel Pharmacy Inc.
Category: homeopathic | Type: HUMAN OTC DRUG LABEL
Date: 20191107

ACTIVE INGREDIENTS: SILVER 6 [hp_X]/1 mL; OXALIS STRICTA WHOLE 6 [hp_X]/1 mL; SUGARCANE 10 [hp_X]/1 mL
INACTIVE INGREDIENTS: WATER; SODIUM CHLORIDE; LACTOSE

Argentum Saccharum Special Order

INDICATIONS AND USAGE

Directions: FOR ORAL USE.

DOSAGE AND ADMINISTRATION

Take the contents of one ampule under the tongue and hold for 30 seconds, then swallow.

ACTIVE INGREDIENT

Active Ingredients: Argentum met. 6X, Oxalis e pl. tota 6X, Saccharum sacch. 10X

Inactive Ingredients: Water, Salt, Lactose

PURPOSE

Use: Temporary relief of headache.

KEEP OUT OF REACH OF CHILDREN.

WARNINGS

Warnings: Claims based on traditional homeopathic practice, not accepted medical evidence. Not FDA evaluated. Do not use if allergic to any ingredient. Consult a doctor before use for serious conditions or if conditions worsen or persist. Contains traces of
lactose. If pregnant or nursing, consult a doctor before use.

QUESTIONS

Questions? Call 866.642.2858 Uriel, East Troy, WI 53120 www.urielpharmacy.com